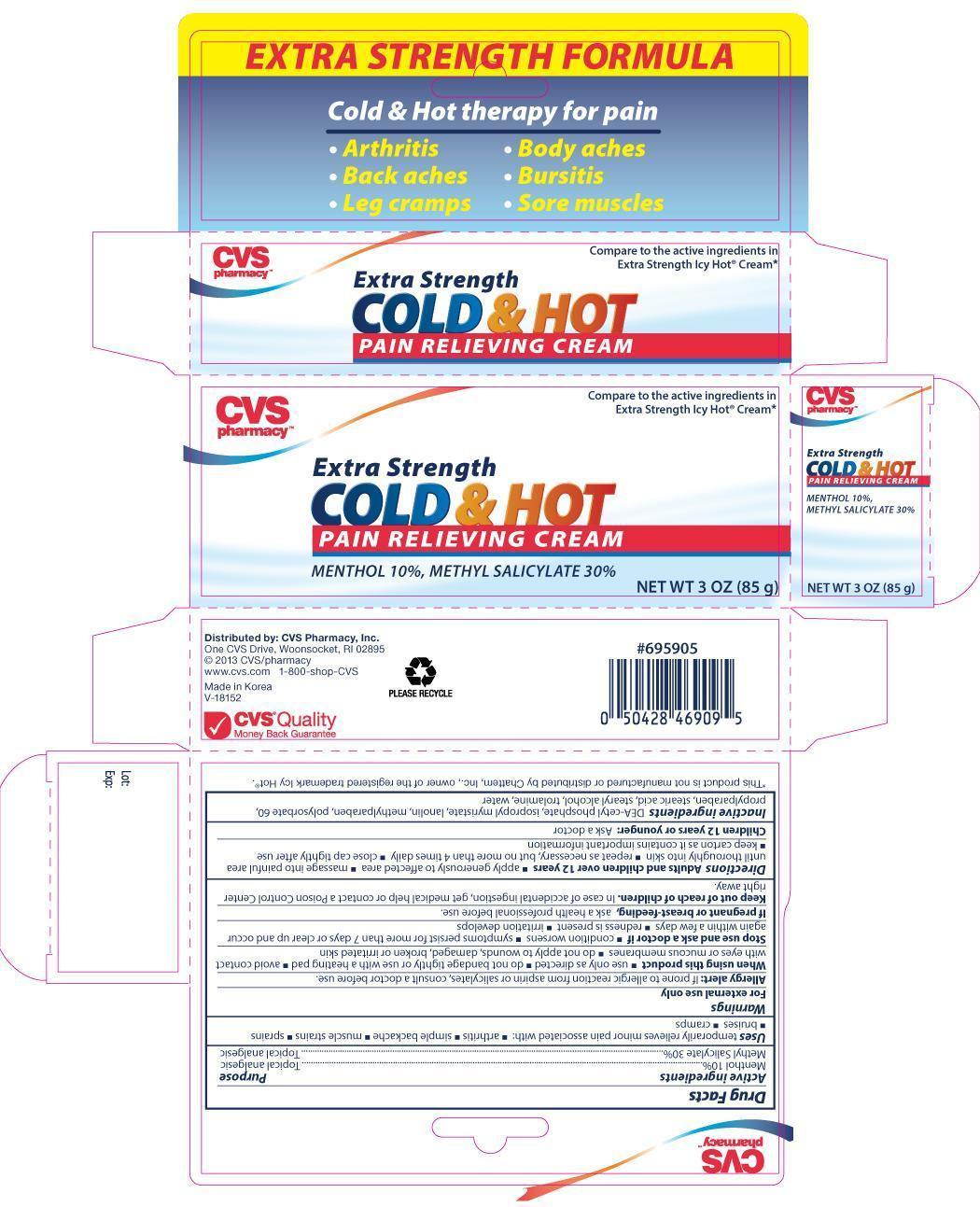 DRUG LABEL: CVS Extra Strength Cold and Hot Pain Relieving
NDC: 59779-469 | Form: CREAM
Manufacturer: CVS
Category: otc | Type: HUMAN OTC DRUG LABEL
Date: 20141013

ACTIVE INGREDIENTS: MENTHOL 10 g/100 g; METHYL SALICYLATE 30 g/100 g
INACTIVE INGREDIENTS: DIETHANOLAMINE CETYL PHOSPHATE; ISOPROPYL MYRISTATE; LANOLIN; METHYLPARABEN; POLYSORBATE 60; PROPYLPARABEN; STEARIC ACID; STEARYL ALCOHOL; TROLAMINE; WATER

Active ingredients Purpose

Menthol 10%..................................................................Topical Analgesic

Methyl Salicylate 30%....................................................Topical Analgesic

PURPOSE

Uses temporarily relieves minor pain associated with:

- arthritis
- simple backache
- muscle strains
- sprains
- bruises
- cramps

Warnings

- For external use only
- Allergy alert: If prone to allergic reaction from aspirin or salicylates, consult a doctor before use.

When using this product

- use only as directed
- do not bandage tightly or use with a heating pad
- avoid contact with eyes or mucous membranes
- do not apply to wounds, damaged, broken or irritated skin

Stop use and ask a doctor if

- condition worsens
- symptoms persist for more than 7 days or clear up and occur again within a few days
- redness is present
- irritation develops

PREGNANCY OR BREAST FEEDING

If pregnant or breast-feeding, ask a health professional before use.

Keep out of reach of children. In case of accidental ingestion, get medical help or contact a Poison Control Center right away.

Directions

- Adults and children over 12 years:
- apply generously to affected area
- massage into painful area until thoroughly into skin
- repeat as necessary, but no more than 4 times daily
- close cap tightly after use
- keep carton as it contains important information
- Children 12 years or younger: Ask a doctor

INACTIVE INGREDIENT

Inactive ingredients DEA-cetyl phosphate, isopropyl myristate, lanolin, methylparaben, polysorbate 60, propylparaben, stearic acid, stearyl alcohol, trolamine, water

DOSAGE AND ADMINISTRATION

Distributed By:

CVS Pharmacy, Inc.

One CVS Drive

Woonsocket, RI 02895

Made in Korea